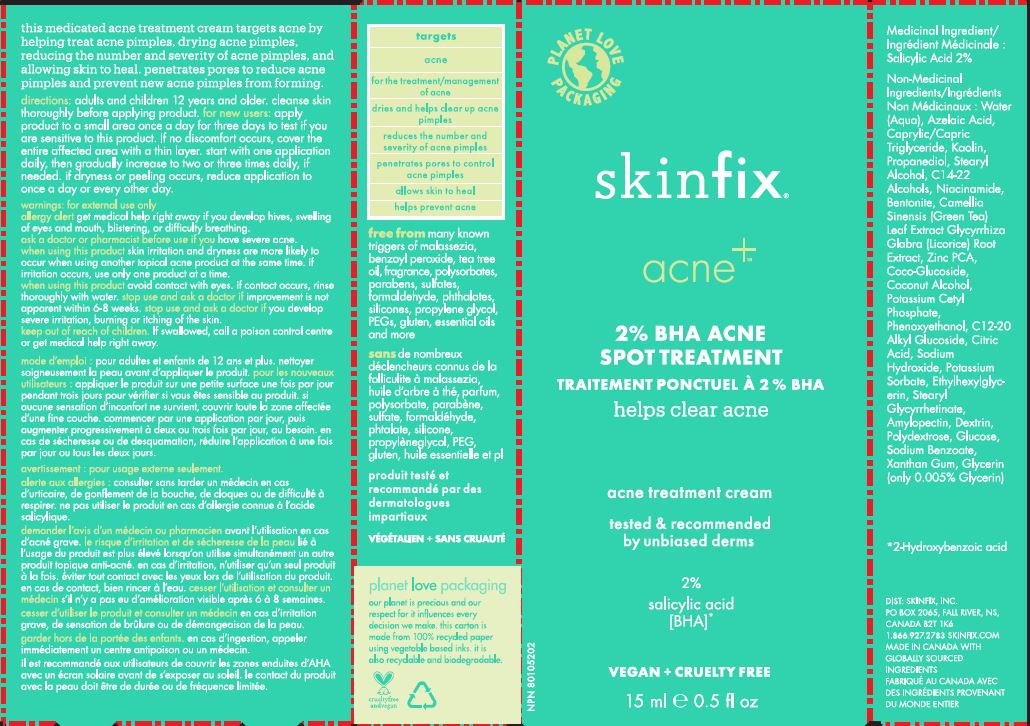 DRUG LABEL: ACNE SPOT TREATMENT
NDC: 61328-404 | Form: CREAM
Manufacturer: Skinfix, Inc.
Category: otc | Type: HUMAN OTC DRUG LABEL
Date: 20260112

ACTIVE INGREDIENTS: SALICYLIC ACID 2 g/100 mL
INACTIVE INGREDIENTS: WATER; MEDIUM-CHAIN TRIGLYCERIDES; AZELAIC ACID; PROPANEDIOL; STEARYL ALCOHOL; KAOLIN; NIACINAMIDE; GLYCYRRHIZA GLABRA; GREEN TEA LEAF; GLYCERIN; BENTONITE; C14-22 ALCOHOLS; POLYDEXTROSE; ICODEXTRIN; AMYLOPECTIN, UNSPECIFIED SOURCE; COCO GLUCOSIDE; ZINC PIDOLATE; STEARYL GLYCYRRHETINATE; ETHYLHEXYLGLYCERIN; XANTHAN GUM; ANHYDROUS CITRIC ACID; POTASSIUM CETYL PHOSPHATE; PHENOXYETHANOL; SODIUM HYDROXIDE; POTASSIUM SORBATE; SODIUM BENZOATE; COCONUT ALCOHOL; ANHYDROUS DEXTROSE; C12-20 ALKYL GLUCOSIDE

SKINFIX - ACNE+ 2% BHA ACNE SPOT TREATMENT

Active Ingredient

SALICYLIC ACID 2%

Purpose

ACNE TREATMENT

USES

HELPS CLEAR ACNE BLEMISHES AND ALLOWS SKIN TO HEAL. HELPS KEEP SKIN CLEAR OF NEW ACNE BLEMISHES. HELPS PREVENT NEW ACNE BLEMISHES FROM FORMING.

WARNINGS

FOR EXTERNAL USE ONLY.

WHEN USING THIS PRODUCT

- SKIN IRRITATION AND DRYNESS IS MORE LIKELY TO OCCUR IF YOU USE ANOTHER TOPICAL ACNE MEDICATION AT THE SAME TIME. IF IRRITATION OCCURS, ONLY USE ONE TOPICAL ACNE MEDICATION AT A TIME.

Keep out of reach of children. If swallowed get medical help or contact a Poison Control Center right away

Directions

APPLY DIRECTLY ONYO BLEMISH OR AFFECTED AREA AFTER CLEANSING 1-2X DAILY.

ALLERGY ALERT DO NOT USE THIS PRODUCT IF YOU HAVE A KNOWN ALLERGY TO SALICYLIC ACID.

Inactive Ingredients

WATER (EAU), KAOLIN, CAPRYLIC/CAPRIC TRIGLYCERIDE, AZELAIC ACID, PROPANEDIOL, STEARYL ALCOHOL, POLYGLYCERYL-2 STEARATE, NIACINAMIDE, GLYCYRRHIZA GLABRA (LICORICE) ROOT EXTRACT, CAMELLIA SINENSIS LEAF EXTRACT, GLYCERIN, BENTONITE, TOCOPHEROL, POLYDEXTROSE, DEXTRIN, AMYLOPECTIN, GLYCERYL STEARATE, ZINC PCA, STEARYL GLYCYRRHETINATE, ETHYLHEXYLGLYCERIN, XANTHAN GUM, CITRIC ACID, POTASSIUM CETYL PHOSPHATE, PHENOXYETHANOL, SODIUM HYDROXIDE, POTASSIUM SORBATE, SODIUM BENZOATE

QUESTIONS?

1.866.927.2783